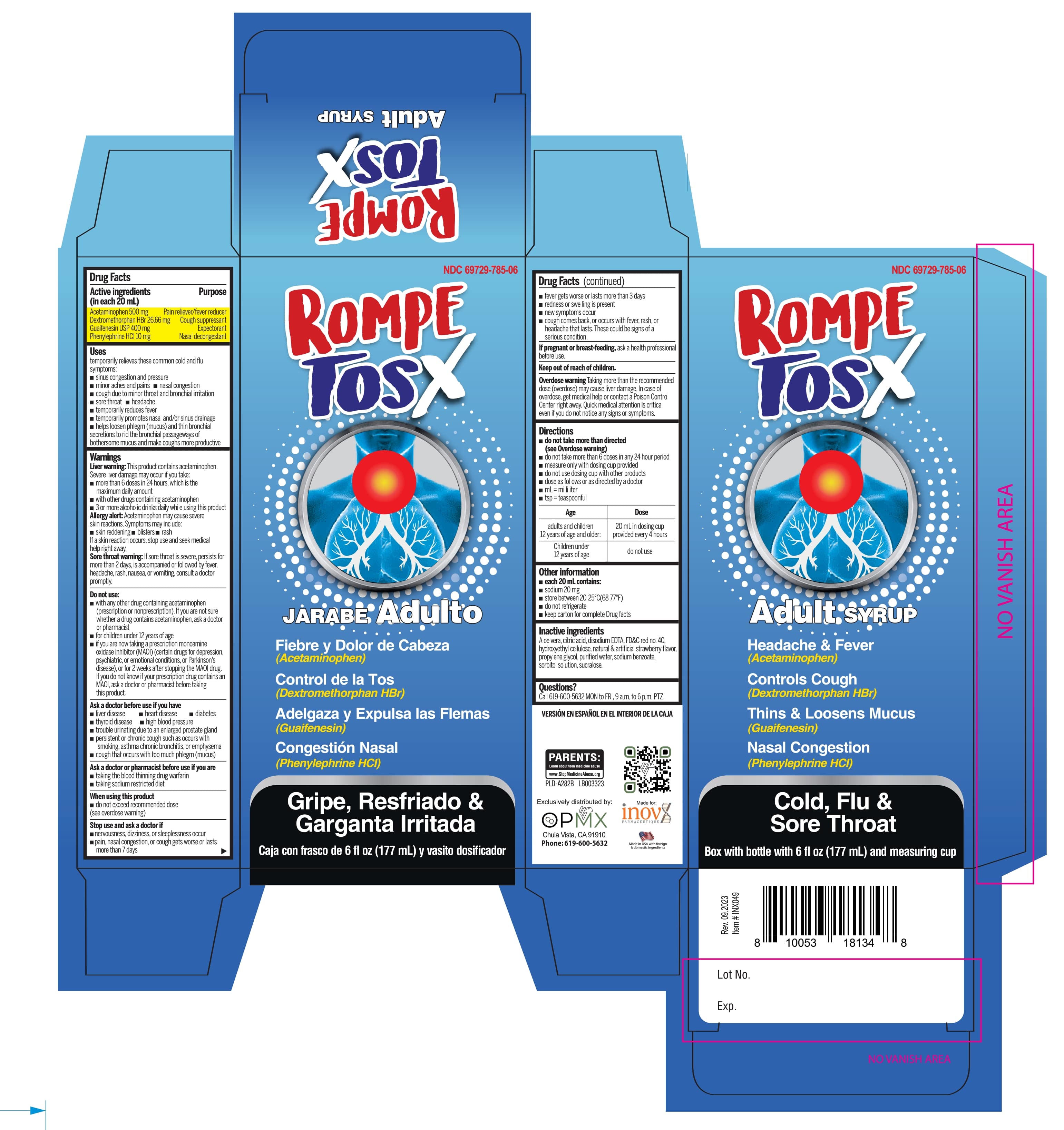 DRUG LABEL: Rompe Tos X Adults
NDC: 69729-785 | Form: SYRUP
Manufacturer: OPMX LLC
Category: otc | Type: HUMAN OTC DRUG LABEL
Date: 20250319

ACTIVE INGREDIENTS: ACETAMINOPHEN 500 mg/20 mL; PHENYLEPHRINE HYDROCHLORIDE 10 mg/20 mL; DEXTROMETHORPHAN HYDROBROMIDE 26.66 mg/20 mL; GUAIFENESIN 400 mg/20 mL
INACTIVE INGREDIENTS: HYDROXYETHYL CELLULOSE, UNSPECIFIED; WATER; ANHYDROUS CITRIC ACID; FD&C RED NO. 40; PROPYLENE GLYCOL; SODIUM BENZOATE; SUCRALOSE; SORBITOL SOLUTION; ALOE; EDETATE DISODIUM

Rompe Tos X Adult

Drug Facts

Active ingredients

Purpose

Active ingredients (in each 20 mL) | Purpose
Acetaminophen 500 mg | Pain reliever/fever reducer
Dextromethorphan HBr 26.66 mg | Cough suppressant
Guaifenesin 400 mg | Expectorant
Phenylephrine HCl 10 mg | Nasal descongestant

Uses

temporarily relieves these common cold/flu symptoms:

- sinus congestion & pressure
- minor aches & pains
- nasal congestion
- cough due to minor throat & bronchial irritation
- sore throat
- headache
- temporarily reduces fever
- temporarily promotes nasal and/or sinus drainage
- helps loosen phlegm (mucus) and thin bronchial secretions to rid the bronchial passageways of bothersome mucus and make coughs more productive.

Warnings

Liver Warning:

This product contains acetaminophen. Severe liver damage may occur if you take:
• more than 6 doses in 24 hrs, which is the maximum daily amount for this product
• with other drugs containing acetaminophen
• 3 or more alcoholic drinks every day while using this product

Allergy Alert:

Acetaminophen may cause severe skin reactions. Symptoms may include:
• skin reddening • blisters • rash
If a skin reaction occurs, stop use and seek medical help right away

Sore throat warning:

If sore throat is severe, persists for more than 2 days, is accompanied or followed by fever, headache, rash, nausea, or vomiting, consult a doctor promptly.

Do not use

- with any other drug containing acetaminophen (prescription or nonprescription). If you are not sure whether a drug contains acetaminophen, ask a doctor or pharmacist.
- for children under 12 years of age
- if you are now taking a prescription monoamine oxidase inhibitor (MAOI) (certain drugs for depression, psychiatric or emotional conditions, or Parkinson's disease), or for 2 weeks after stopping the MAOI drug. If you do not know if your prescription drug contains an MAOI, ask a doctor or pharmacist before taking this product.

Ask a doctor before use if you have

- liver disease
- heart disease
- diabetes
- thyroid disease
- high blood pressure
- trouble urinating due to enlarged prostate gland
- persistent or chronic cough sush as smoking, asthma, chronic bronchitis, or emphysema
- cough that occurs with too much phlegm (mucus)

Ask a doctor or pharmacist before use if you are

- taking the blood thinning drug warfarin
- taking sodium restricted diet

When using this product

- do not exceed recommended dose (see overdose warning)

Stop use and ask a doctor if

- nervousness, dizziness or sleeplessness occur
- pain, nasal congestion or cough gets worse or lasts more than 7 days
- fever gets worse or lasts more than 3 days
- redness or swelling is present
- new symptoms occur
- cough comes back or occurs with rash or headache that lasts.

These could be signs of a serious condition.

If pregnant or breast-feeding,

ask a health professional before use.

Overdose warning

Taking more than recommended dose (overdose) may cause liver damaage. In case of overdose, get medical help or contact a Poison Control Center right away. Quick medical attention is critical for adults & for children even if you do not notice any signs or symptoms.

Directions

- do not take more than directed (see Overdose warning)
- do not take more than 6 doses in any 24 hour period
- measure only with dosing cup provided
- do not use dosing cup with other products
- dose as follows or as directed by a doctor
- mL = milliliter
- tsp = teaspoonful

Age | Dose
adults and children 12 years of age and older | 20 mL in dosing cup provided every 4 hours
Children under 12 years of age | do not use

Other information

- each 20 mL contains
- sodium 20 mg
- Store between 20-25°C (68-77°F)
- do not refrigerate
- keep carton for complete Drug facts

Inactive ingredients

Aloe vera, citric acid, disodium EDTA, FD&C red no. 40, hydroxyethyl cellulose, natural & artificial strawberry flavor, propylene glycol, purified water, sodium benzoate, sorbitol solution, sucralose

Questions?

Call 616-600-5632 MON to FRI, 9 a.m. to 6 p.m. PTZ

PRINCIPAL DISPLAY PANEL - 177 mL Bottle Label

NDC 69729-785-06

Rompe Tos X

6 fl oz (177 mL)